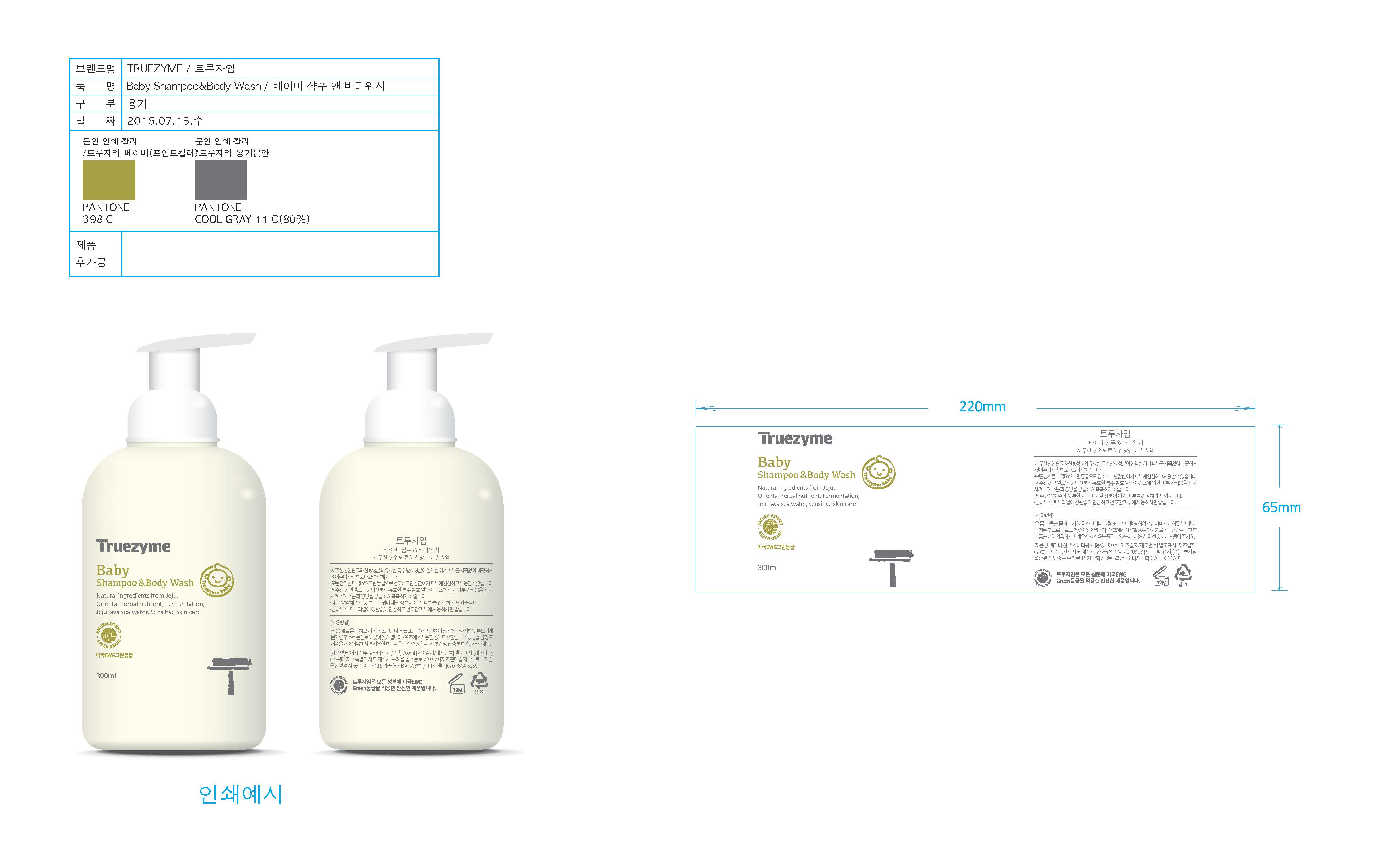 DRUG LABEL: Truezyme Baby ShampooAndBody Wash
NDC: 71076-0002 | Form: LIQUID
Manufacturer: Truezyme Co., Ltd.
Category: otc | Type: HUMAN OTC DRUG LABEL
Date: 20161115

ACTIVE INGREDIENTS: GLYCERIN 3.5 g/100 mL
INACTIVE INGREDIENTS: WATER; PANTHENOL

ACTIVE INGREDIENT

Glycerin

PURPOSE

Cleanse, moisturize, and smoothen sensitive baby's skin gently.

INACTIVE INGREDIENT

Sea Water, Water, Lauryl Glucoside, Decyl Glucoside, Pentylene Glycol, Laminaria Japonica Extract, Glycyrrhiza Glabra (Licorice) Root Extract, Butylene Glycol, Panthenol, etc.

WARNINGS

1. Stop using the product if there are any of the following abnormal symptoms appearing after use and consult with your dermatologist as continued use can worsen the symptoms.

1) If there are red spots, swelling, itchiness, or irritation

2) If the above symptoms appear around the skin to which the product has been applied after being exposed to direct sunlight.

2. Do not apply the product to any parts of the skin with wound, eczema, or dermatitis.

3. If it gets into eye, wash the eye with clean water immediately.

4. Wash away with water enough after use since not enough rinsing can lead to hair loss or discoloration.

5. Those who are allergic to certain medicinal herb, such as pollen and tangerine, must stop using the product if they experience hypersensitivity. 6. Precautions on storage and handling

1) Make sure to close the cap after use.

2) Keep out of the reach of children.

3) Do not keep the product in a hot or cold place or a place getting direct sunlight.

INDICATIONS AND USAGE

- Wet the whole body and lather well on a shower sponge, a towel, or hands and massage the whole body gently and wash away with water cleanly.

- For a bath, you can enjoy a refreshing enzymatic bath by lathering enough in warm water.

* Shake well before use.

Keep out of reach of children.

DOSAGE AND ADMINISTRATION

For the external use only